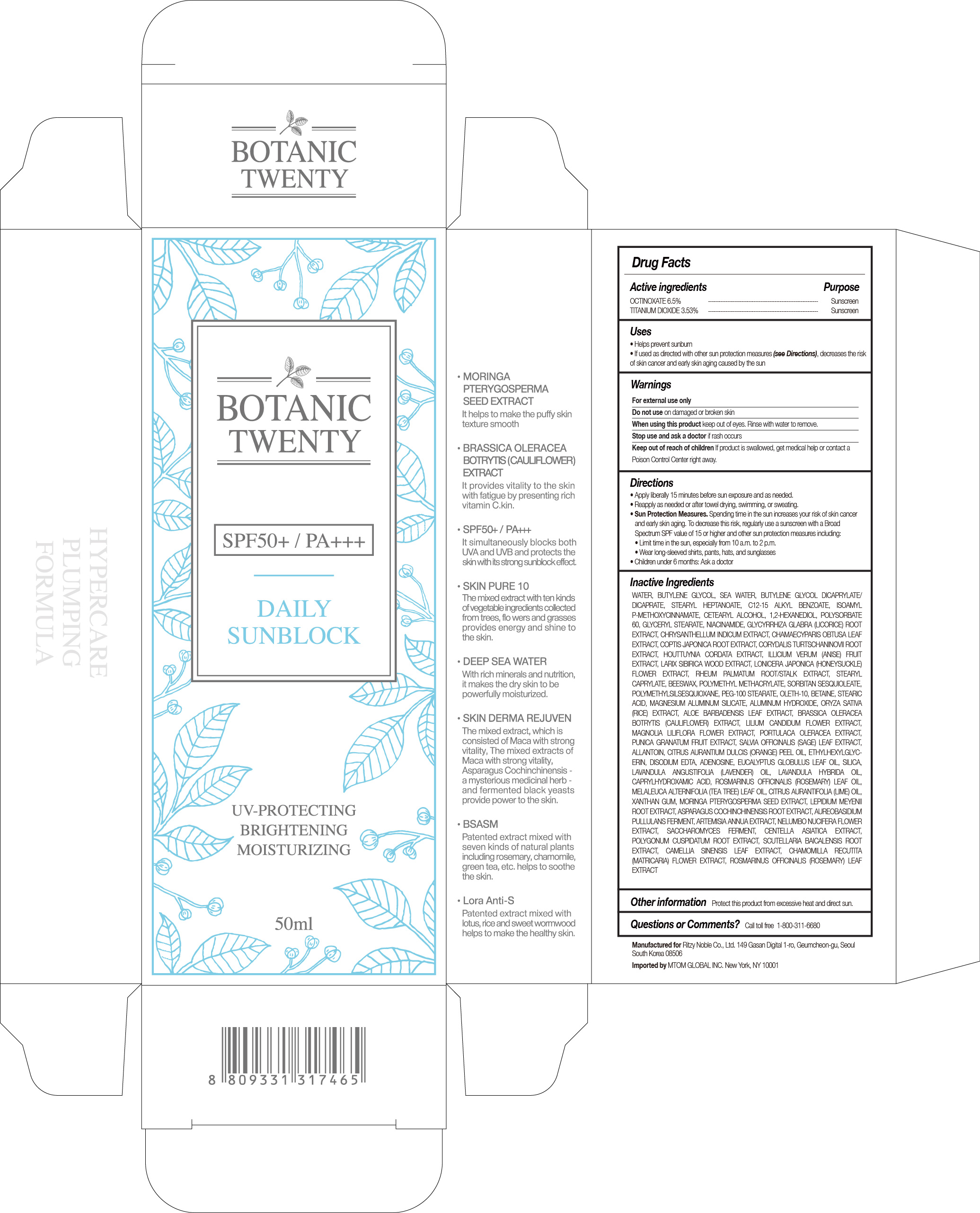 DRUG LABEL: BOTANIC TWENTY DAILY SUNBLOCK SPF50
NDC: 71364-004 | Form: LOTION
Manufacturer: RITZY NOBLE CO., LTD.
Category: otc | Type: HUMAN OTC DRUG LABEL
Date: 20180101

ACTIVE INGREDIENTS: OCTINOXATE 3.25 g/50 mL; TITANIUM DIOXIDE 1.765 g/50 mL
INACTIVE INGREDIENTS: ALKYL (C12-15) BENZOATE; AMILOXATE; GLYCERYL MONOSTEARATE; CHRYSANTHELLUM INDICUM WHOLE; CHAMAECYPARIS OBTUSA LEAF; STAR ANISE FRUIT; STEARYL CAPRYLATE; SORBITAN SESQUIOLEATE; CETOSTEARYL ALCOHOL; 1,2-HEXANEDIOL; POLYSORBATE 60; YELLOW WAX; POLY(METHYL METHACRYLATE; 450000 MW); STEARYL HEPTANOATE; NIACINAMIDE; COPTIS JAPONICA ROOT; LARIX SIBIRICA WOOD; LONICERA JAPONICA FLOWER; RHEUM PALMATUM ROOT; BUTYLENE GLYCOL DICAPRYLATE/DICAPRATE; GLYCYRRHIZA GLABRA; CORYDALIS TURTSCHANINOVII WHOLE; HOUTTUYNIA CORDATA WHOLE; WATER; BUTYLENE GLYCOL

Botanic Twenty Daily Sunblock SPF50+ / PA+++

DRUG FACTS

ACTIVE INGREDIENTS

OCTINOXATE 6.5%

TITANIUM DIOXIDE 3.53%

PURPOSE

Sunscreen

USES

• Helps prevent sunburn
• If used as directed with other sun protection measures (see Directions), decreases the risk of skin cancer and early skin aging caused by the sun

WARNINGS

For external use only

When using this product keep out of eyes. Rinse with water to remove.

STOP USE

Stop use and ask a doctor if rash occurs

Keep out of reach of children. If product is swallowed, get medical help or contact a Poison Control Center right away.

DIRECTIONS

• Apply liberally 15 minutes before sun exposure and as needed.
• Reapply as needed or after towel drying, swimming, or sweating.
• Sun Protection Measures. Spending time in the sun increases your risk of skin cancer
and early skin aging. To decrease this risk, regularly use a sunscreen with a Broad
Spectrum SPF value of 15 or higher and other sun protection measures including:
• Limit time in the sun, especially from 10 a.m. to 2 p.m.
• Wear long-sleeved shirts, pants, hats, and sunglasses
• Children under 6 months: Ask a doctor

INACTIVE INGREDIENTS

WATER, BUTYLENE GLYCOL, SEA WATER, BUTYLENE GLYCOL DICAPRYLATE/DICAPRATE, STEARYL HEPTANOATE, C12-15 ALKYL BENZOATE, ISOAMYL P-METHOXYCINNAMATE, CETEARYL ALCOHOL, 1,2-HEXANEDIOL, POLYSORBATE 60, GLYCERYL STEARATE, NIACINAMIDE, GLYCYRRHIZA GLABRA (LICORICE) ROOT EXTRACT, CHRYSANTHELLUM INDICUM EXTRACT, CHAMAECYPARIS OBTUSA LEAF EXTRACT, COPTIS JAPONICA ROOT EXTRACT, CORYDALIS TURTSCHANINOVII ROOT EXTRACT, HOUTTUYNIA CORDATA EXTRACT, ILLICIUM VERUM (ANISE) FRUIT EXTRACT, LARIX SIBIRICA WOOD EXTRACT, LONICERA JAPONICA (HONEYSUCKLE) FLOWER EXTRACT, RHEUM PALMATUM ROOT/STALK EXTRACT, STEARYL CAPRYLATE, BEESWAX, POLYMETHYL METHACRYLATE, SORBITAN SESQUIOLEATE, POLYMETHYLSILSESQUIOXANE, PEG-100 STEARATE, OLETH-10, BETAINE, STEARIC ACID, MAGNESIUM ALUMINUM SILICATE, ALUMINUM HYDROXIDE, ORYZA SATIVA (RICE) EXTRACT, ALOE BARBADENSIS LEAF EXTRACT, BRASSICA OLERACEA BOTRYTIS (CAULIFLOWER) EXTRACT, LILIUM CANDIDUM FLOWER EXTRACT, MAGNOLIA LILIFLORA FLOWER EXTRACT, PORTULACA OLERACEA EXTRACT, PUNICA GRANATUM FRUIT EXTRACT, SALVIA OFFICINALIS (SAGE) LEAF EXTRACT, ALLANTOIN, CITRUS AURANTIUM DULCIS (ORANGE) PEEL OIL, ETHYLHEXYLGLYCERIN, DISODIUM EDTA, ADENOSINE, EUCALYPTUS GLOBULUS LEAF OIL, SILICA, LAVANDULA ANGUSTIFOLIA (LAVENDER) OIL, LAVANDULA HYBRIDA OIL, CAPRYLHYDROXAMIC ACID, ROSMARINUS OFFICINALIS (ROSEMARY) LEAF OIL, MELALEUCA ALTERNIFOLIA (TEA TREE) LEAF OIL, CITRUS AURANTIFOLIA (LIME) OIL, XANTHAN GUM, MORINGA PTERYGOSPERMA SEED EXTRACT, LEPIDIUM MEYENII ROOT EXTRACT, ASPARAGUS COCHINCHINENSIS ROOT EXTRACT, AUREOBASIDIUM PULLULANS FERMENT, ARTEMISIA ANNUA EXTRACT, NELUMBO NUCIFERA FLOWER EXTRACT, SACCHAROMYCES FERMENT, CENTELLA ASIATICA EXTRACT, POLYGONUM CUSPIDATUM ROOT EXTRACT, SCUTELLARIA BAICALENSIS ROOT EXTRACT, CAMELLIA SINENSIS LEAF EXTRACT, CHAMOMILLA RECUTITA (MATRICARIA) FLOWER EXTRACT, ROSMARINUS OFFICINALIS (ROSEMARY) LEAF EXTRACT

OTHER INFORMATION

Protect this product from excessive heat and direct sun.

QUESTIONS OR COMMENTS?

Call toll free 1-800-311-6680